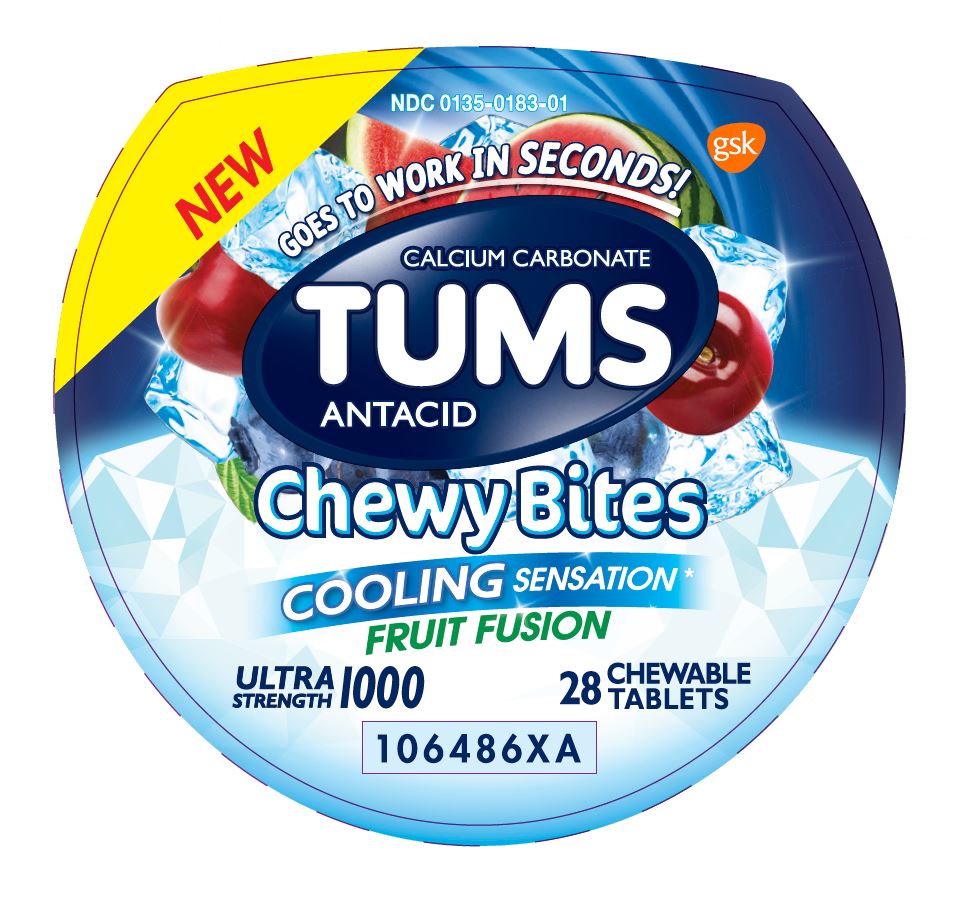 DRUG LABEL: Tums Chewy Bites
NDC: 0135-0183 | Form: TABLET, CHEWABLE
Manufacturer: Haleon US Holdings LLC
Category: otc | Type: HUMAN OTC DRUG LABEL
Date: 20240302

ACTIVE INGREDIENTS: CALCIUM CARBONATE 1000 mg/1 1
INACTIVE INGREDIENTS: PROPYLPARABEN; WATER; ALCOHOL; AMMONIA; YELLOW WAX; CARNAUBA WAX; CITRIC ACID MONOHYDRATE; COCONUT OIL; STARCH, CORN; CORN SYRUP; ICODEXTRIN; ETHYL ACETATE; FD&C BLUE NO. 1; FD&C RED NO. 40; FD&C YELLOW NO. 5; FD&C YELLOW NO. 6; ACACIA; ISOPROPYL ALCOHOL; LECITHIN, SOYBEAN; MALTODEXTRIN; MEDIUM-CHAIN TRIGLYCERIDES; METHYLPARABEN; MODIFIED CORN STARCH (1-OCTENYL SUCCINIC ANHYDRIDE); BUTYL ALCOHOL; PHOSPHORIC ACID; POVIDONE, UNSPECIFIED; PROPYLENE GLYCOL; SHELLAC; SODIUM BENZOATE; SORBIC ACID; SORBITOL; SOYBEAN OIL; SUCROSE; TERT-BUTYLHYDROQUINONE; TITANIUM DIOXIDE; CORN OIL

Drug Facts

Active ingredient (per tablet)

Calcium Carbonate 1000 mg

Purpose

Antacid

Uses

relieves

- heartburn
- acid indigestion
- sour stomach
- upset stomach associated with these symptoms

Warnings

Ask a doctor or pharmacist before use if you are

presently taking a prescription drug. Antacids may interact with certain prescription drugs.

When using this product

- do not take more than 4 tablets in 24 hours
- if pregnant do not take more than 4 tablets in 24 hours
- do not use the maximum dosage for more than 2 weeks except under the advice and supervision of a doctor

Directions

- adults and children 12 years of age and over:chew 2-3 tablets as symptoms occur, or as directed by a doctor
- do not take for symptoms that persist for more than 2 weeks unless advised by a doctor

Other Information

- each chewable tablet contains:elemental calcium 400mg
- do not store above 25°C (77°F)

Inactive Ingredients (2 ct. Pouch)

alcohol, ammonium hydroxide, beeswax, carnauba wax, citric acid, coconut oil, corn starch, corn syrup, dextrin, ethyl acetate, FD&C blue no.1 aluminum lake, FD&C red no. 40*, FD&C red no. 40 aluminum lake, FD&C yellow no. 5 aluminum lake (tartrazine)*, FD&C yellow no. 6 aluminum lake, flavors, gum arabic, isopropyl alcohol, lecithin, maltodextrin, medium chain triglycerides, methylparaben*, modified starch, n-butyl alcohol, phosphoric acid*, polyvinylpyrrolidone*, propylene glycol, propylparaben*, purified water, shellac, sodium benzoate*, sorbic acid, sorbitol, soybean oil, sucrose, tert-butylhydroquinone, titanium dioxide, vegetable oil

*contains one or more of these ingredients

Inactive Ingredients (28 ct. Bottle)

alcohol, ammonium hydroxide, beeswax, carnauba wax, citric acid, coconut oil, corn starch, corn syrup, dextrin, ethyl acetate, FD&C blue no.1 aluminum lake, FD&C red no. 40, FD&C red no. 40 aluminum lake, FD&C yellow no. 5 aluminum lake (tartrazine), FD&C yellow no. 6 aluminum lake, flavors, gum arabic, isopropyl alcohol, lecithin, maltodextrin, medium chain triglycerides, methylparaben, modified starch, n-butyl alcohol, phosphoric acid, polyvinylpyrrolidone, propylene glycol, propylparaben, purified water, shellac, sodium benzoate, sorbic acid, sorbitol, soybean oil, sucrose, tert-butylhydroquinone, titanium dioxide, vegetable oil

Questions?

Call 1-800-897-7535

Principal Display Panel

NEW

NDC 0135-0183-01

TUMS

CALCIUM CARBONATE

ANTACID

Chewy Bites

COOLING SENSATION*

FRUIT FUSION

GOES TO WORK IN SECONDS!

ULTRA STRENGTH 1000

28 CHEWABLE TABLETS

*Cooling sensation refers only to our unique cooling flavor(s).

Do not use if printed inner safety seal under cap is broken or missing.

Dist. by: GSKConsumer Healthcare

Warren, NJ 07059

Trademarks are owned by or licensed to the GSK group of companies.

©2018 GSK or its licensor.

106487XA